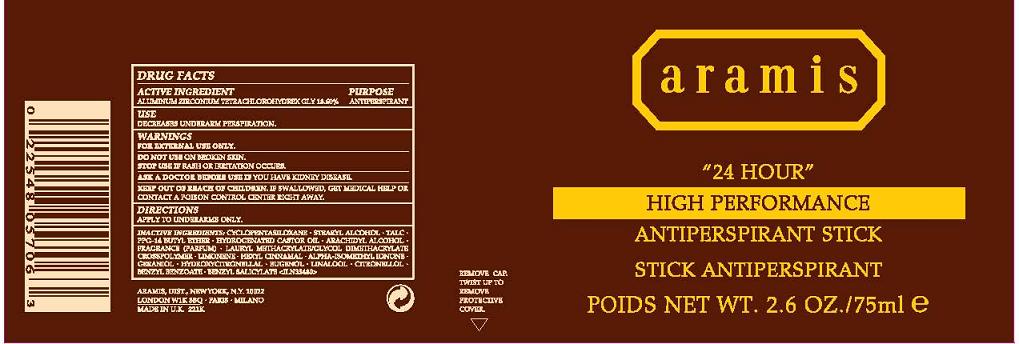 DRUG LABEL: 24 HOUR HIGH PERFORMANCE ANTIPERSPIRANT
NDC: 42472-695 | Form: STICK
Manufacturer: ARAMIS INC.
Category: otc | Type: HUMAN OTC DRUG LABEL
Date: 20110711

ACTIVE INGREDIENTS: ALUMINUM ZIRCONIUM TETRACHLOROHYDREX GLY  18.6 mL/100 mL
INACTIVE INGREDIENTS: CYCLOMETHICONE 5; STEARYL ALCOHOL; HYDROGENATED CASTOR OIL; ARACHIDYL ALCOHOL; TALC; PPG-14 BUTYL ETHER

ACTIVE INGREDIENT

ALUMINUM ZIRCONIUM TETRACHLOROHYDREX-GLY 18.6%

INACTIVE INGREDIENT

INACTIVE INGREDIENTS: CYCLOPENTASILOXANE [] STEARYL ALCOHOL [] TALC [] PPG-14 BUTYL ETHER [] HYDROGENATED CASTOR OIL [] ARACHIDYL ALCOHOL [] FRAGRANCE (PARFUM) [] LAURYL METHACRYLATE/GLYCOL DIMETHACRYLATE CROSSPOLYMER

PURPOSE: ANTIPERSPIRANT

INDICATIONS AND USAGE

USE: REDUCES UNDERARM WETNESS

WARNINGS:

- FOR EXTERNAL USE ONLY
- DO NOT USE ON BROKEN SKIN
- STOP USE IF IRRITATION OCCURS

ASK A DOCTOR BEFORE USE IF YOU HAVE KIDNEY DISEASE.

KEEP OUT OF REACH OF CHILDREN. IF SWALLOWED, GET MEDICAL HELP OR CONTACT A POISON CONTROL CENTER IMMEDIATELY.

DOSAGE AND ADMINISTRATION

DIRECTIONS: APPLY TO UNDERARMS ONLY

PACKAGE LABEL

PRINCIPAL DISPLAY PANEL:

ARAMIS

24 HOUR

HIGH PERFORMANCE

ANTIPERSPIRANT STICK

NT WT 2.6 OZ/ 75 ML

ARAMIS DISTR,

NY, NY 10022